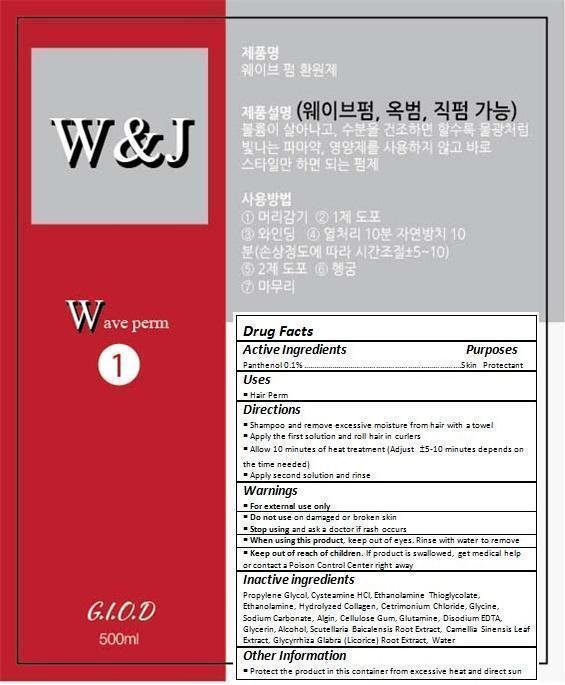 DRUG LABEL: ELF Perm
NDC: 70072-003 | Form: CREAM
Manufacturer: giod Co.
Category: otc | Type: HUMAN OTC DRUG LABEL
Date: 20150905

ACTIVE INGREDIENTS: PANTHENOL 0.47 g/479.39 g
INACTIVE INGREDIENTS: PROPYLENE GLYCOL; CYSTEAMINE HYDROCHLORIDE; MONOETHANOLAMINE THIOGLYCOLATE; MONOETHANOLAMINE; CETRIMONIUM CHLORIDE; GLYCINE; SODIUM CARBONATE; SODIUM ALGINATE; CARBOXYMETHYLCELLULOSE SODIUM, UNSPECIFIED FORM; GLUTAMINE; EDETATE DISODIUM; GLYCERIN; ALCOHOL; SCUTELLARIA BAICALENSIS ROOT; GREEN TEA LEAF; GLYCYRRHIZA GLABRA; WATER

Drug Facts

ACTIVE INGREDIENT

Panthenol 0.1%

PURPOSE

Hair Perm

INDICATIONS AND USAGE

Shampoo and remove excessive moisture from hair with a towel
Apply the first solution and roll hair in curlers
Allow 10 minutes of heat treatment (Adjust ±5-10 minutes depends on the time needed)
Apply second solution and rinse

DOSAGE AND ADMINISTRATION

Shampoo and remove excessive moisture from hair with a towel
Apply the first solution and roll hair in curlers
Allow 10 minutes of heat treatment (Adjust ±5-10 minutes depends on the time needed)
Apply second solution and rinse

WARNINGS

For external use only.
Do not use on damaged or broken skin.
When using this product, keep out of eyes. Rinse with water to remove.
Stop using and ask a doctor if rash occurs.

KEEP OUT OF REACH OF CHILDREN

Keep out of reach of the children. If product is swallowed, get medical help or contact a poison control center right away.

INACTIVE INGREDIENT

Propylene Glycol, Cysteamine HCl, Ethanolamine Thioglycolate, Ethanolamine, Hydrolyzed Collagen, Cetrimonium Chloride, Glycine, Sodium Carbonate, Algin, Cellulose Gum, Glutamine, Disodium EDTA, Glycerin, Alcohol, Scutellaria Baicalensis Root Extract, Camellia Sinensis Leaf Extract, Glycyrrhiza Glabra (Licorice) Root Extract, Water